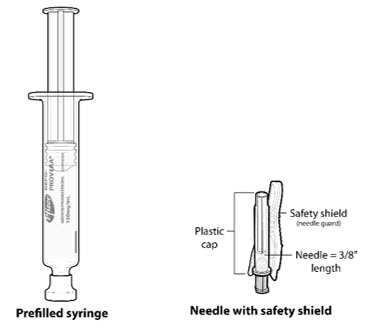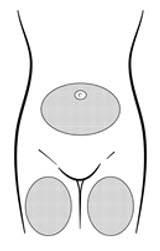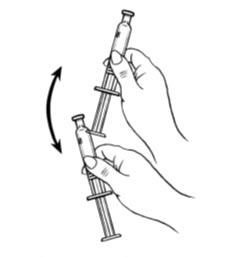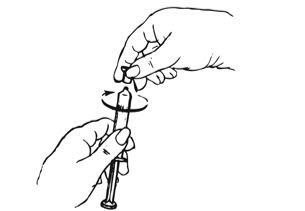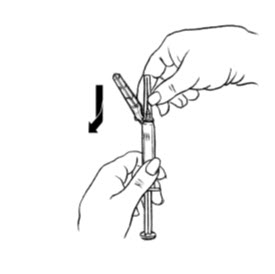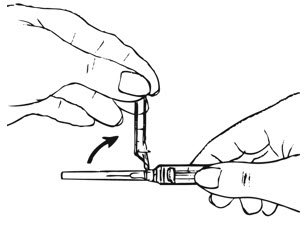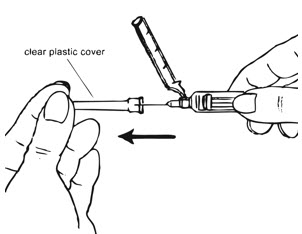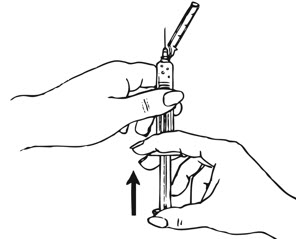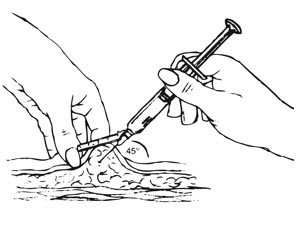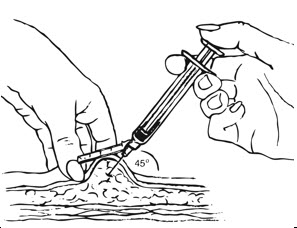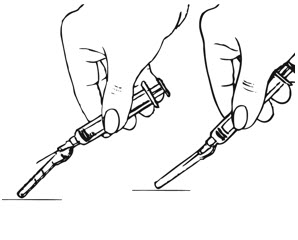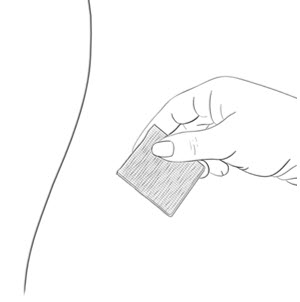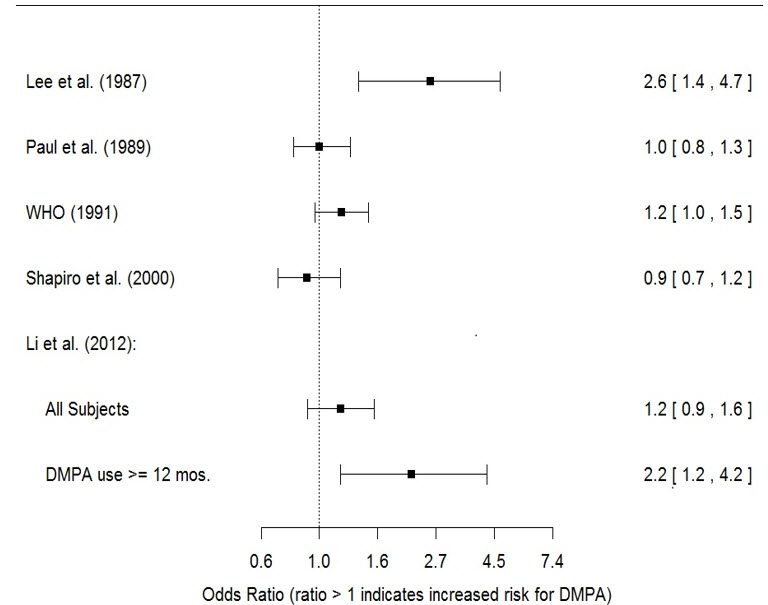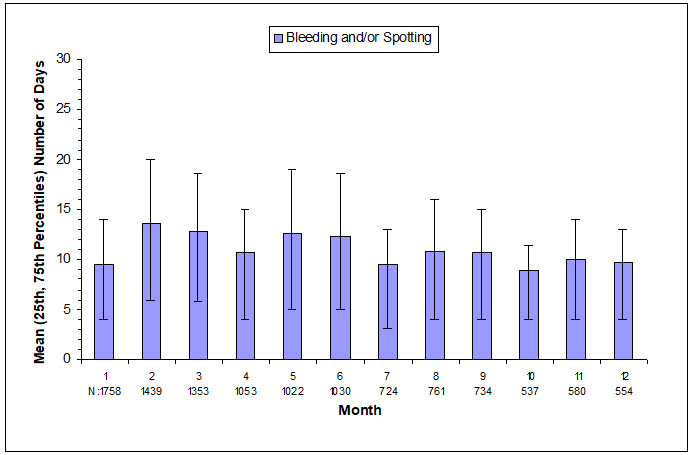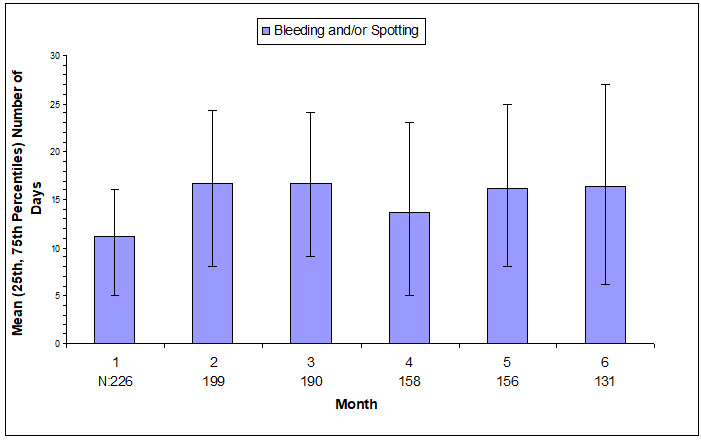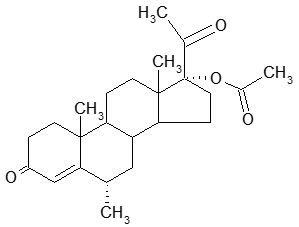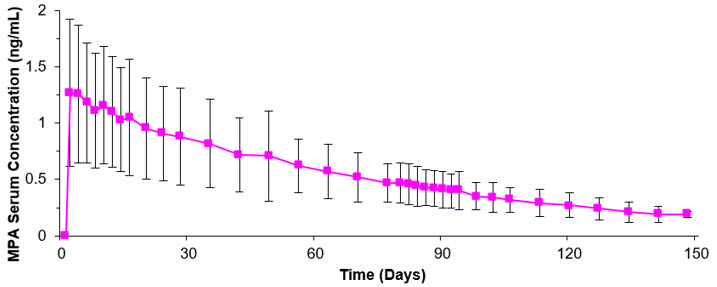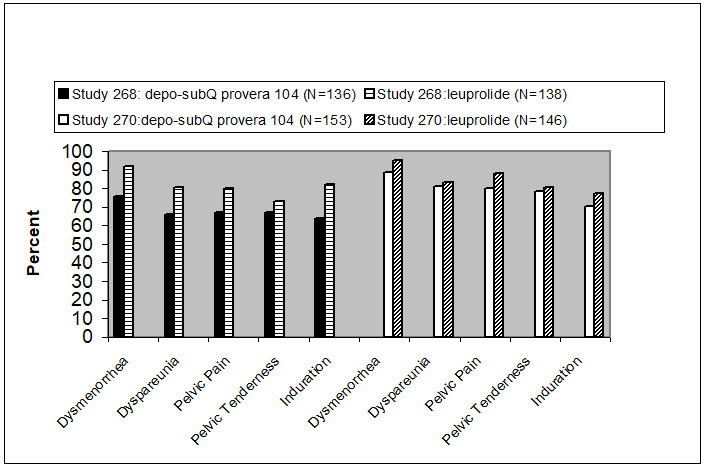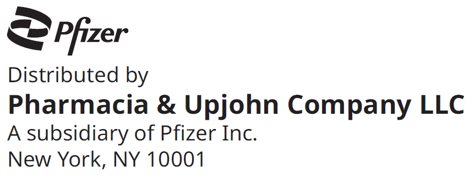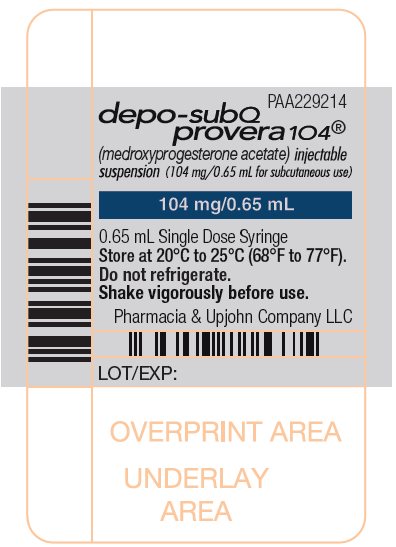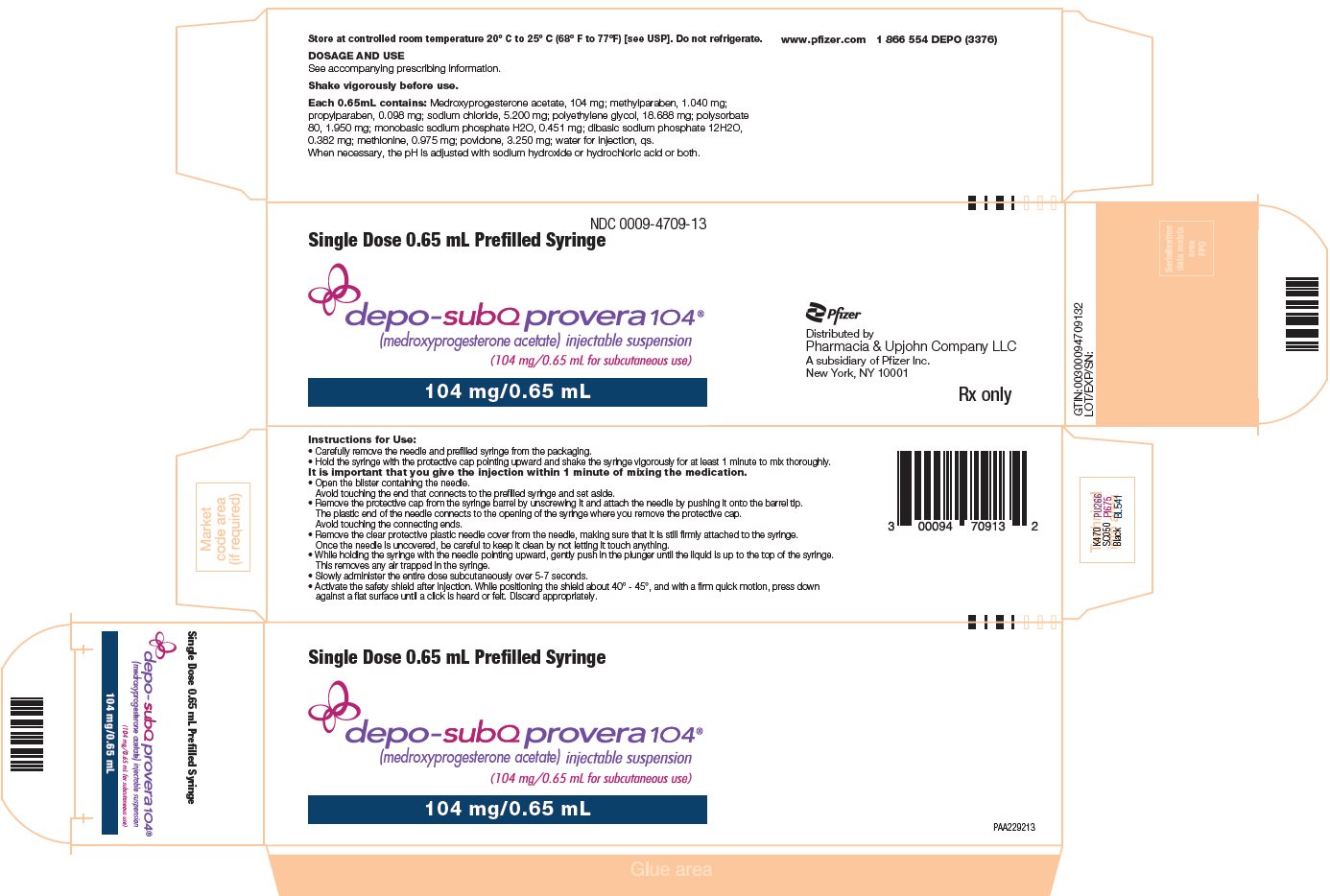 DRUG LABEL: Depo-SubQ Provera
NDC: 0009-4709 | Form: INJECTION, SUSPENSION
Manufacturer: Pharmacia & Upjohn Company LLC
Category: prescription | Type: HUMAN PRESCRIPTION DRUG LABEL
Date: 20251218

ACTIVE INGREDIENTS: MEDROXYPROGESTERONE ACETATE 104 mg/0.65 mL
INACTIVE INGREDIENTS: METHYLPARABEN 1.04 mg/0.65 mL; PROPYLPARABEN 0.098 mg/0.65 mL; SODIUM CHLORIDE 5.2 mg/0.65 mL; POLYETHYLENE GLYCOL, UNSPECIFIED 18.688 mg/0.65 mL; POLYSORBATE 80 1.95 mg/0.65 mL; SODIUM PHOSPHATE, MONOBASIC, ANHYDROUS 0.451 mg/0.65 mL; SODIUM PHOSPHATE, DIBASIC, ANHYDROUS 0.382 mg/0.65 mL; METHIONINE 0.975 mg/0.65 mL; POVIDONE, UNSPECIFIED 3.25 mg/0.65 mL; WATER; SODIUM HYDROXIDE; HYDROCHLORIC ACID

HIGHLIGHTS OF PRESCRIBING INFORMATION

These highlights do not include all the information needed to use DEPO-SUBQ PROVERA 104® safely and effectively. See full prescribing information for DEPO-SUBQ PROVERA 104.
DEPO-SUBQ PROVERA 104 (medroxyprogesterone acetate) injectable suspension, for subcutaneous use
Initial U.S. Approval: 1959

RECENT MAJOR CHANGES

Warnings and Precautions, Meningioma (5.4) | 12/2025

WARNING: LOSS OF BONE MINERAL DENSITY

See full prescribing information for complete boxed warning.

- Women who use depo-subQ provera 104 may lose significant bone mineral density. Bone loss is greater with increasing duration of use and may not be completely reversible. (5.1)
- It is unknown if use of depo-subQ provera 104 during adolescence or early adulthood, a critical period of bone accretion, will reduce peak bone mass and increase the risk for osteoporotic fracture in later life. (5.1)
- Depo-subQ provera 104 is not recommended as a long-term (i.e., longer than 2 years) birth control method or medical therapy for endometriosis-associated pain unless other options are considered inadequate. (1, 5.1)

1 INDICATIONS AND USAGE

Depo-subQ provera 104 is a progestin that is indicated in females of reproductive age for:

- Prevention of pregnancy. (1)
- Management of endometriosis-associated pain. (1)

Limitations of Use:

Use of depo-subQ provera 104 is not recommended as a long-term (i.e., longer than 2 years) birth control method or medical therapy for endometriosis-associated pain unless other options are considered inadequate. (1, 5.1)

2 DOSAGE AND ADMINISTRATION

- Only for healthcare professional administration. (2.1)
- Prior to first injection, confirm the patient is not pregnant. (2.1)
- Administer 104 mg of depo-subQ provera 104 by subcutaneous injection into the anterior thigh or abdomen, once every 12 to 14 weeks. (2.1)
- See Full Prescribing Information for recommendations on switching from another contraceptive method to depo-subQ provera 104. (2.2)
- See Full Prescribing Information for important preparation and administration instructions. (2.3)

3 DOSAGE FORMS AND STRENGTHS

Injectable suspension: 104 mg/0.65 mL (3)

4 CONTRAINDICATIONS

- Active thrombophlebitis, or current or history of thromboembolic disorders, or cerebral vascular disease. (4)
- Known, suspected, or past malignancy of the breast. (4)
- Significant liver disease. (4)
- Known hypersensitivity to medroxyprogesterone acetate or any of the ingredients of depo-subQ provera 104. (4)
- Undiagnosed vaginal bleeding. (4)

5 WARNINGS AND PRECAUTIONS

- Thromboembolic disorders: Discontinue depo-subQ provera 104 in patients who develop arterial or venous thrombosis. (5.2)
- Breast cancer risks: Monitor women with a family history of breast cancer or a significant risk of breast cancer carefully. (5.3)
- Meningioma: Discontinue depo-subQ provera 104 if meningioma is diagnosed. Monitor patients for signs and symptoms of meningioma. (5.4)
- Ectopic pregnancy: Consider ectopic pregnancy if a woman becomes pregnant or complains of severe abdominal pain. (5.5)
- Anaphylaxis: Provide emergency medical treatment. (5.6)
- Injection site reactions (e.g., persistent atrophy, dimpling/indentation, lump/nodule and discoloration) have been reported. (5.11)
- Diabetics may be at greater risk of hyperglycemia. (5.13)
- Jaundice and elevated transaminase: Discontinue depo-subQ provera 104 if jaundice or elevated transaminase levels develop. (5.14)

6 ADVERSE REACTIONS

Most common adverse reactions (incidence >5%) are dysfunctional uterine bleeding, headache, increased weight, amenorrhea, and injection site reactions. (6.1)

To report SUSPECTED ADVERSE REACTIONS, contact Pfizer Inc. at 1-800-438-1985 or FDA at 1-800-FDA-1088 or www.fda.gov/medwatch.

7 DRUG INTERACTIONS

Strong CYP3A inhibitors and inducers: Avoid concomitant use. (7)

8 USE IN SPECIFIC POPULATIONS

- Pregnancy: Discontinue if pregnancy occurs. (8.1)
- Lactation: Detectable amounts of drug have been identified in the milk of mothers receiving depot-medroxyprogesterone acetate. (8.2)
- Pediatric patients (after menarche): Bone loss is a particular concern. (8.4)

FULL PRESCRIBING INFORMATION

WARNING: LOSS OF BONE MINERAL DENSITY

- Women who use depo-subQ provera 104 may lose significant bone mineral density. Bone loss is greater with increasing duration of use and may not be completely reversible [see Warnings and Precautions (5.1)].
- It is unknown if use of depo-subQ provera 104 during adolescence or early adulthood, a critical period of bone accretion, will reduce peak bone mass and increase the risk for osteoporotic fracture in later life [see Warnings and Precautions (5.1)].
- Depo-subQ provera 104 is not recommended as a long-term (i.e., longer than 2 years) birth control method or medical therapy for endometriosis-associated pain unless other options are considered inadequate [see Indications and Usage (1) and Warnings and Precautions (5.1)].

1 INDICATIONS AND USAGE

Depo-subQ provera 104 is indicated in females of reproductive age for:

- Prevention of pregnancy and
- Management of endometriosis-associated pain.

Limitations of Use:

The use of depo-subQ provera 104 is not recommended as a long-term (i.e., longer than 2 years) birth control method or medical therapy for endometriosis-associated pain unless other options are considered inadequate [see Dosage and Administration (2.1) and Warnings and Precautions (5.1)].

2 DOSAGE AND ADMINISTRATION

2.1 Important Dosage and Administration Instructions

Depo-subQ provera 104 is only for subcutaneous administration and is only to be administered by a healthcare professional.

Use for longer than 2 years is not recommended (unless other birth control methods or medical therapies for endometriosis-associated pain are considered inadequate) due to the impact of long-term depo-subQ provera 104 treatment on bone mineral density (BMD) [see Warnings and Precautions (5.1)].

Prior to the first injection confirm that the patient is not pregnant. For women who are sexually active and who have regular menses, administer the first injection only during the first 5 days of a normal menstrual period. For women who are breast-feeding, administer the first injection during or after the sixth post-partum week.

The recommended dosage of depo-subQ provera 104 is 104 mg given subcutaneously every 12 to 14 weeks. If more than 14 weeks elapse between injections, confirm that the patient is not pregnant before the next injection. Instruct the patient that if they are unable to receive an injection within 12–14 weeks, another contraceptive method should be used until the next depo-subQ provera 104 injection. The dosage does not need to be adjusted for body weight.

Inject the entire contents of the pre-filled syringe using strict aseptic technique into the upper anterior thigh or abdomen, rotating the sites with every injection [see Dosage and Administration (2.3)].

2.2 Switching from Another Method of Contraception

When switching from another contraceptive method to depo-subQ provera 104, administer depo-subQ provera 104 in a manner that ensures continuous contraceptive coverage. Follow the respective recommendations when switching from the contraceptive methods listed below:

- Combined hormonal contraceptives: administer the first injection of depo-subQ provera 104 within 7 days after the last day of using the combined hormonal contraceptive method (i.e., within 7 days after taking the last active pill).
- An implant: administer the first injection of depo-subQ provera 104 on the day of implant removal.
- A contraceptive vaginal ring or transdermal system: administer the first injection of depo-subQ provera 104 on the day the patient would have inserted the next ring or applied the next transdermal system.
- An Intrauterine Device (IUD) or Intrauterine System (IUS): administer the first injection of depo-subQ provera 104 on the day of IUD/IUS removal. If the IUD/IUS is not removed on the first day of the patient's menstrual cycle, instruct patients to use a non-hormonal back-up method of birth control for the first 7 days after administration of depo-subQ provera 104.
- Depot medroxyprogesterone acetate injectable suspension for intramuscular use (DMPA-IM): inject depo-subQ provera 104 12 to 14 weeks after the last dose of DMPA-IM.

2.3 Preparation and Administration Instructions

Prior to injection:

- Ensure all the components in Figure A are available and that depo-subQ provera 104 is at room temperature.
- Shake the pre-filled syringe vigorously prior to injection to ensure appropriate viscosity of the suspension.
- Inspect depo-subQ provera 104 visually for particulate matter and discoloration.
  Figure A. Components in the Package

Step 1: Select & Prepare the Injection Area

- Select a preferred injection area, i.e., the left or right upper thigh or the abdomen (see shaded areas, Figure B).
- Avoid selection of bony areas and the umbilicus.
- Clean the skin in the injection area you have chosen with a clean cotton pad or clean paper tissue.
- Rotate the injection site by injecting into a different puncture site than used for the previous injection.

Figure B.
Preferred injection areas:
Left or right upper thigh or abdomen

Step 2: Prepare Syringe

- Carefully remove the needle and syringe from the packaging.
- Hold the syringe firmly by the barrel, with the barrel pointing upward.
- Shake the syringe vigorously for at least 1 minute to mix thoroughly (Figure C).

Figure C.
Shake vigorously for 1 minute

- While holding the syringe barrel firmly, remove the protective cap from the tip of the syringe barrel by unscrewing it (Figure D).

Figure D.

- While holding the syringe barrel firmly, attach the needle to the barrel of the syringe firmly by pushing the plastic needle cover down fully and firmly with a slight twisting movement (Figure E).

Figure E.

- Move the safety shield away from the needle and toward the syringe barrel. The safety shield will remain in an open 45- to 90-degree position (Figure F).

Figure F.

- While holding the syringe barrel firmly, remove the plastic needle cover from the needle without twisting, ensuring the needle is still firmly attached to the syringe (Figure G).

Figure G.

- While holding the syringe with the needle pointing upward, gently push in the plunger until the liquid is up to the top of the syringe (Figure H). There should be no air within the barrel.

Figure H.

Step 3: Injecting depo-Sub Q provera 104

- Gently grasp and squeeze a large area of skin in the chosen injection area between the thumb and forefinger, pulling it away from the body (Figure I).
- Insert the needle at a 45-degree angle so that most of the needle is in the fatty tissue.
- The plastic hub of the needle should be nearly or almost touching the skin.

Figure I.

Inject slowly until the syringe is empty (Figure J).

- This should take about 5 to 7 seconds.
- It is important that the entire dose is given.

Figure J.
Inject slowly
(5–7 seconds)

Step 4: Remove the Needle and Activate the Safety Shield

- After completing the injection, remove the needle from the skin and activate the safety shield as follows:
  - While positioning the shield about 40°– 45°, and with a firm quick motion, press down against a flat surface until a click is heard or felt (Figure K).
  - If uncertain that the safety shield is fully engaged, repeat this step.

Figure K.

- Use a clean cotton pad to press lightly on the injection area for a few seconds (Figure L).
- Do not rub the area.

Figure L.

3 DOSAGE FORMS AND STRENGTHS

Injectable suspension (104 mg/0.65 mL) in a single-dose pre-filled syringe, packaged with a 26-gauge × 3/8-inch Terumo SurGuard® needle.

4 CONTRAINDICATIONS

The use of depo-subQ provera 104 is contraindicated in the following conditions:

- Active thrombophlebitis, or current or history of thromboembolic disorders, or cerebral vascular disease [see Warnings and Precautions (5.2)].
- Known, suspected, or past malignancy of the breast [see Warnings and Precautions (5.3)].
- Significant liver disease [see Warnings and Precautions (5.14)].
- Known hypersensitivity to medroxyprogesterone acetate or any of the ingredients in depo-subQ provera 104 [see Warnings and Precautions (5.6)].
- Undiagnosed vaginal bleeding [see Warnings and Precautions (5.12)].

5 WARNINGS AND PRECAUTIONS

5.1 Loss of Bone Mineral Density

Use of depo-subQ provera 104 reduces serum estrogen levels and is associated with significant loss of bone mineral density (BMD). This loss of BMD is of particular concern during adolescence and early adulthood, a critical period of bone accretion. It is unknown if use of depo-subQ provera 104 by younger women will reduce peak bone mass and increase the risk for osteoporotic fracture in later life.

A study to assess the reversibility of loss of BMD in adolescents was conducted with DMPA-IM. After discontinuing DMPA-IM in these adolescents, mean BMD loss at the total hip and femoral neck did not fully recover by 5 years (60 months) post-treatment in the sub-group of adolescents who were treated for more than 2 years [see Clinical Studies (14.4)]. Similarly, in adults, there was only partial recovery of mean BMD at the total hip, femoral neck, and lumbar spine towards baseline by 2 years post-treatment [see Clinical Studies (14.3)].

The use of depo-subQ provera 104 is not recommended as a long-term (i.e., longer than 2 years) birth control method or medical therapy for endometriosis-associated pain unless other options are considered inadequate. BMD should be evaluated when a woman needs to continue to use depo-subQ provera 104 long-term. In adolescents, interpretation of BMD results should take into account patient age and skeletal maturity.

Other birth control methods or therapies for endometriosis-associated pain should be considered in the risk/benefit analysis for the use of depo-subQ provera 104 in women with osteoporosis risk factors. Depo-subQ provera 104 can pose an additional risk in patients with risk factors for osteoporosis (e.g., metabolic bone disease, chronic alcohol and/or tobacco use, anorexia nervosa, strong family history of osteoporosis, or chronic use of drugs that can reduce bone mass such as anticonvulsants or corticosteroids).

5.2 Arterial and Venous Thromboembolic Disorders

There have been reports of serious arterial and venous thrombotic events in women treated with DMPA-IM. Women with a history of thromboembolic disorders were not studied in clinical trials of depo-subQ provera 104. Although no causal relationship between the use of depo-subQ provera 104 and thrombotic events has been clearly established, patients who develop arterial or venous thrombosis while taking depo-subQ provera 104 should discontinue treatment.

Do not re-administer depo-subQ provera 104 pending examination if there is a sudden onset of a suspected vascular ocular event (e.g., partial or complete loss of vision, proptosis, or diplopia) or migraine. Do not re-administer depo-subQ provera 104 if examination reveals papilledema or retinal vascular lesions.

5.3 Cancer Risks

Breast Cancer

The use of hormonal contraceptives, including depo sub-Q provera 104, is contraindicated in women who have or have had breast cancer because breast cancer may be sensitive to hormones [see Contraindications (4)]. Women who have a family history of breast cancer or a significant risk of breast cancer should be monitored.

The results of five large case-control studies assessing the association between DMPA-IM use and the risk of breast cancer are summarized in Figure M. Three of the studies suggest a slightly increased risk of breast cancer in the overall population of users; these increased risks were statistically significant in one study. One US study^1 evaluated the timing and duration of use and found a statistically significant increased risk of breast cancer in recent DMPA-IM users (defined as last use within the past five years) who used DMPA-IM for 12 months or longer; this is consistent with results of a previous study^2.

Figure M. Risk Estimates of Breast Cancer in DMPA-IM Users

Odds Ratio [95% confidence interval (CI)] displayed on logarithmic scale

Odds ratio estimates were adjusted for the following covariates:
Lee et al. (1987): age, parity, and socioeconomic status.
Paul et al. (1989): age, parity, ethnic group, and year of interview.
WHO (1991): age, center, and age at first live birth.
Shapiro et al. (2000): age, ethnic group, socioeconomic status, and any combined estrogen/progestogen oral contraceptive use.
Li et al. (2012): age, year, BMI, duration of OC use, number of full-term pregnancies, family history of breast cancer, and history of
screening mammography.

Based on the published SEER-18 2015 incidence rate (age-adjusted to the 2000 US Standard Population) of breast cancer for US women, all races, age 20 to 49 years, a doubling of risk would increase the incidence of breast cancer in women who use DMPA-IM from about 73 to about 146 cases per 100,000 women.

Other Cancers

The relative rate of invasive squamous-cell cervical cancer in women who ever used DMPA-IM was estimated to be 1.11 (95% CI: 0.96 to 1.29). No trends in risk with duration of use or times since initial or most recent exposure were observed.

Long-term, case-controlled surveillance of users of DMPA-IM found no overall increased risk of ovarian or liver cancer.

5.4 Meningioma

Cases of meningiomas have been reported following repeated administration of medroxyprogesterone acetate, primarily with long term use. Monitor patients on depo-subQ provera 104 for signs and symptoms of meningioma. Discontinue depo-subQ provera 104 if a meningioma is diagnosed.

5.5 Ectopic Pregnancy

Healthcare professionals should be alert to the possibility of an ectopic pregnancy among women using depo-subQ provera 104 who become pregnant or complain of severe abdominal pain.

5.6 Anaphylaxis

Serious anaphylactic reactions have been reported in women using depo-subQ provera 104. If an anaphylactic reaction occurs, appropriate emergency medical treatment should be administered.

5.7 Fluid Retention

Because progestational drugs including depo-subQ provera 104 may cause fluid retention, monitor patients with conditions that might be affected by fluid retention.

5.8 Weight Gain

Weight gain is a common occurrence in women using depo-subQ provera 104. In three large clinical trials using depo-subQ provera 104, the mean weight gain was 3.5 lb (1.6 kg) in the first year of use. In a small, two-year study comparing depo-subQ provera 104 to DMPA-IM, the mean weight gain observed for women using depo-subQ provera 104 [7.5 lb (3.4 kg)] was similar to the mean weight gain for women using DMPA-IM [7.6 lb (3.5 kg)].

Although there are no data related to weight gain beyond 2 years for depo-subQ provera 104, the data on DMPA-IM may be relevant. In a clinical study, after five years, 41 women using Depo-Provera CI (150 mg) had a mean weight gain of 11.2 lb (5.1 kg), while 114 women using non-hormonal contraception had a mean weight gain of 6.4 lb (2.9 kg).

5.9 Delayed Return of Ovulation or Fertility

Return to ovulation is likely to be delayed after stopping depo-subQ provera 104, as demonstrated in a study of 15 women who received multiple doses of depo-subQ provera 104:

- Median time to ovulation was 10 months after the last injection.
- Earliest return to ovulation was 6 months after the last injection.
- 12 women (80%) ovulated within 1 year of the last injection.

However, ovulation has occurred as early as 14 weeks after a single dose of depo-subQ provera 104; therefore, administer the next depo-subQ provera 104 12 to 14 weeks after the last injection.

Return to fertility also is likely to be delayed after stopping therapy. Among 28 women using depo-subQ provera 104 for contraception who stopped treatment to become pregnant, 7 women were lost to follow-up. One woman became pregnant within one year of her last injection and another woman became pregnant 443 days after her last injection. The remaining 19 women had not become pregnant; it is not known if these 19 women were still attempting to become pregnant or if they had started a new contraceptive method.

5.10 Depression

Depression (3% of depo-subQ provera 104-treated patients) and other mood disorders have been reported in clinical trials of depo-subQ provera 104 [see Adverse Reactions (6.1)]. Patients with a history of depression or who are on treatment for depression may be at increased risk for depression recurrence or exacerbation and for associated mood disorders while receiving depo-subQ provera 104. Therefore, patients should be monitored for symptoms of depression and mood changes.

5.11 Injection Site Reactions

In five clinical studies of depo-subQ provera 104 involving 2325 women (282 treated for up to 6 months, 1780 treated for up to 1 year, and 263 women treated for up to 2 years), 5% of women reported injection site reactions (such as pain/tenderness, nodule/lump, lipodystrophy, discoloration), and 1% had persistent atrophy/indentation/dimpling [see Adverse Reactions (6.1)]. These injection site reactions have also been reported in post-marketing experience.

5.12 Bleeding Irregularities

Most women using depo-subQ provera 104 experienced changes in menstrual bleeding patterns, such as amenorrhea, irregular unpredictable spotting or bleeding, prolonged spotting or bleeding, or heavy bleeding [see Adverse Reactions (6.1)]. Fewer women experienced irregular bleeding and more experienced amenorrhea with longer term use of depo‑subQ provera 104, consistent with expected endometrial thinning effects.

In three contraception trials, 39% of 2053 depo-subQ provera 104-treated women experienced amenorrhea during Month 6, and 57% experienced amenorrhea during Month 12. In two endometriosis trials using depo-subQ provera 104, 24% of 289 women experienced amenorrhea during Month 6 [see Adverse Reactions (6.1)].

If abnormal bleeding is persistent or severe, evaluate the patient for underlying pathology or pregnancy.

5.13 Risk of Hyperglycemia in Patients with Diabetes

Some patients receiving progestins may exhibit a decrease in glucose tolerance; therefore, patients with diabetes may be at greater risk of hyperglycemia.

5.14 Jaundice and Elevated Transaminase

Discontinue depo-subQ provera 104 if jaundice or elevated transaminase levels develop. Depo-subQ provera 104 may be resumed after both the jaundice and elevated transaminase levels resolve, and the healthcare professional determines that depo-subQ provera 104 did not cause the abnormalities.

5.15 Protection Against Sexually Transmitted Infections

Patients should be counseled that this product does not protect against HIV infection (including AIDS) and other sexually transmitted infections.

6 ADVERSE REACTIONS

The following important adverse reactions are described in more detail in other sections of the prescribing information:

- Loss of bone mineral density [see Warnings and Precautions (5.1)]
- Arterial and venous thromboembolic disorders [see Warnings and Precautions (5.2)]
- Anaphylaxis [see Warnings and Precautions (5.6)]
- Fluid retention [see Warnings and Precautions (5.7)]
- Delayed return of ovulation or fertility [see Warnings and Precautions (5.9)]
- Depression [see Warnings and Precautions (5.10)]
- Injection site reactions [see Warnings and Precautions (5.11)]
- Bleeding irregularities [see Warnings and Precautions (5.12)]

6.1 Clinical Trials Experience

Clinical trials are conducted under widely varying conditions, therefore adverse reaction rates observed in the clinical trials of a drug cannot be directly compared to rates in the clinical trials of another drug and may not reflect the rates observed in practice.

The data described below reflect exposure to depo-subQ provera 104 in five clinical trials involving 2325 women including 2043 women who received treatment for contraception (1780 treated up to 1 year and 263 treated for up to 2 years) and 282 women for endometriosis for up to 6 months. In these pooled trials, 9% of women discontinued treatment due to an adverse reaction and the most common reason for discontinuation was dysfunctional uterine bleeding (3%).

Adverse Reactions in the Contraception Adult Studies

Table 1 presents frequently reported adverse reactions (>1%) in the contraception pooled studies. In these studies, the most frequently reported adverse reactions (>5%) were dysfunctional uterine bleeding (e.g., irregular, increased, decreased, or spotting), headache, increased weight, amenorrhea, and injection site reactions (e.g., pain/tenderness, nodule/lump, persistent atrophy/indentation/dimpling or lipodystrophy).

The frequency reported is based on the all-causality incidence in the pooled results of the three contraception studies. Closely related "Adverse Reaction" terms were grouped but individual patients reporting two or more grouped events were only counted once.

Table 1. Frequently Reported Adverse Reactions in the Contraception Studies (>1%)
Adverse Reaction | Frequency
Dysfunctional uterine bleeding (irregular, increase, decrease, spotting) | 18%
Headache | 9%
Increased weight (see below) | 7%
Amenorrhea | 6%
Injection site reactions (such as pain/tenderness, nodule/lump, persistent atrophy/indentation/dimpling, lipodystrophy, discoloration) | 6%
Vaginitis, including candidiasis and bacterial | 5%
Abdominal pain | 4%
Urinary tract infections | 4%
Acne | 4%
Depression | 3%
Decreased libido | 3%
Nausea | 3%
Back pain | 3%
Breast pain/tenderness | 2%
Fatigue | 2%
Anxiety | 1%
Irritability | 1%
Dizziness | 1%

Dysfunctional Uterine Bleeding

The extent of bleeding and spotting in the three contraception trials is presented in Figure N; data from the endometriosis trials are presented in Figure O [see Warnings and Precautions (5.1)].

Figure N. Mean Number of Bleeding or Spotting Days in the Subgroup of Women with Bleeding or Spotting Among Women Treated with depo-subQ provera 104 in Contraception Studies

N=Number of subjects with bleeding or spotting during indicated month.

Figure O. Mean Number of Bleeding or Spotting Days in the Subgroup of Women with Bleeding or Spotting Among Women Treated with depo-subQ provera 104 in Endometriosis Studies

N=Number of subjects with bleeding or spotting during indicated month.

Weight Gain

In three large clinical trials, the mean weight gain in depo-subQ provera 104 treated patients was 3.5 lb (1.6 kg) in the first year of use. Half (50%) of women remained within 4.9 lb (2.2 kg) of their initial body weight; 12% of women lost more than 4.9 lb (2.2 kg), and 38% of women gained more than 5.1 lb (2.3 kg). In a small, 2-year study comparing depo-subQ provera 104 to DMPA-IM, the mean weight gain observed for women using depo-subQ provera 104 [7.5 lb (3.4 kg)] was similar to the mean weight gain for women using DMPA-IM [7.7 lb (3.5 kg)].

Other Adverse Reactions Observed in Contraception Clinical Trials with depo-subQ provera 104

Other adverse reactions occurring at an incidence of <1% in women who received depo-subQ provera 104 were as follows:

- Neoplasms benign, malignant and unspecified (including cysts and polyps): breast lump
- Blood and lymphatic system disorders: anemia
- Immune system disorders: drug hypersensitivity
- Metabolism and nutrition disorders: weight decreased, fluid retention
- Nervous system disorders: facial palsy, syncope, paresthesia, somnolence
- Cardiac disorders: tachycardia
- Vascular disorders: hot flushes
- Respiratory, thoracic and mediastinal disorders: asthma, dyspnea
- Gastrointestinal disorders: diarrhea, abdominal distension
- Skin and subcutaneous tissue disorders: urticaria, pruritus, dry skin
- Reproductive system and breast disorders: dysmenorrhea, galactorrhea, dyspareunia
- General disorders and administration site conditions: chest pain

Adverse Reactions in the Endometriosis Adult Studies

The safety profile of depo-subQ provera 104 in endometriosis clinical trials was similar to the safety profile of depo-subQ provera 104 in the contraception studies with the exception of the following adverse reactions which were more frequently reported in patients with endometriosis: abdominal pain, diarrhea, nausea, and back pain.

In endometriosis studies, subjects recorded daily the occurrence and severity of hot flushes. Of the depo-subQ provera 104 users, 29% reported experiencing moderate or severe hot flushes at baseline, 36% at Month 3, and 27% at Month 6. Of the leuprolide users, 33% reported experiencing moderate or severe hot flushes at baseline, 74% at Month 3, and 69% at Month 6.

Adverse Reactions in the Adolescent Contraception Study

Depo-sub-Q provera 104 and DMPA-IM clinical trials reported similar safety profiles in adult study populations (see Table 1 above). Accordingly, a similar safety profile is expected for adolescents receiving depo-subQ provera 104 as for adolescents receiving DMPA-IM.

The safety profile of DMPA-IM for prevention of pregnancy in adolescents was observed to be generally similar to the safety profile of adult women using DMPA-IM for prevention of pregnancy, with the exception of the following adverse reactions which were reported more frequently by adolescents: abdominal pain, diarrhea, back pain, weight increased, depression, headache, and dysmenorrhea.

6.2 Postmarketing Experience

The following adverse reactions have been identified during post-approval use of DMPA-IM. Because these reactions are reported voluntarily from a population of uncertain size, it is not possible to reliably estimate their frequency or establish a causal relationship to drug exposure:

- Immune system disorders: anaphylactic reaction, anaphylactoid reaction, angioedema
- Vascular disorders: pulmonary embolism, deep vein thrombosis, thrombophlebitis
- Musculoskeletal and connective tissue disorders: osteoporosis (including osteoporotic fractures)
- Reproductive system and breast disorders: prolonged anovulation, unexpected pregnancy, uterine hyperplasia
- Respiratory, thoracic and mediastinal disorders: hoarseness
- Skin and subcutaneous tissue disorders: increased body odor
- Gastrointestinal disorders: gastrointestinal disturbances
- General disorders and administration site conditions: axillary swelling, chills, thirst

7 DRUG INTERACTIONS

7.1 Effect of Other Drugs on depo-SubQ provera 104

Moderate or Strong CYP3A Inducers

Concomitant use with moderate or strong CYP3A inducers may decrease concentrations of medroxyprogesterone acetate which may reduce depo-subQ provera 104 efficacy. This effect is based upon the primary metabolism of medroxyprogesterone acetate by CYP3A and was not confirmed by a clinical study.

Avoid coadministration of depo-subQ provera 104 with moderate or strong CYP3A inducers. Some examples of moderate CYP3A inducers are bosentan, efavirenz, etravirine, and modafinil. Some examples of strong CYP3A inducers are rifampin, carbamazepine, phenytoin, phenobarbital, mitotane, and St. John's wort (the CYP3A4 induction effect of St. John's wort varies widely and is preparation dependent). These examples are a guide and do not represent a comprehensive list of all possible drugs that may fit these categories.

The use of CYP3A inducers may require using a back-up or alternate contraceptive method.

8 USE IN SPECIFIC POPULATIONS

8.1 Pregnancy

Risk Summary

There is no use for contraception in pregnancy; therefore, depo-subQ provera 104 should be discontinued during pregnancy.

Epidemiologic studies and meta-analyses have not found an increased risk of genital or non-genital birth defects (including cardiac anomalies and limb-reduction defects) following exposure to progestins before conception or during early pregnancy.

All pregnancies have a background risk of birth defect, loss, or other adverse outcomes. In the U.S. general population, the estimated background risk of major birth defects and miscarriage in clinically recognized pregnancies is 2-4% and 15‑20%, respectively.

8.2 Lactation

Risk Summary

Although medroxyprogesterone acetate is detectable in the milk of mothers receiving DMPA-IM, milk composition, quality, and amount do not appear to be adversely affected. Effects on milk production and lactation initiation/duration remain unclear when administered before 6 weeks after delivery, therefore, in mothers who exclusively breastfeed, initiate depo-subQ provera 104 during or after the sixth post-partum week [see Dosage and Administration (2.1)].

No adverse effects in breastfed infants would be expected with maternal use of progestins. Neonates and infants exposed to medroxyprogesterone acetate from breast milk have been studied and no adverse effects have been noted.

The developmental and health benefits of breast-feeding should be considered along with the mother’s clinical need for depo-subQ provera 104 and any potential adverse effects on the breastfed child from depo-subQ provera 104 or from the underlying maternal condition.

8.3 Females and Males of Reproductive Potential

Depo-subQ provera 104 is indicated for the prevention of pregnancy and would therefore be expected to impair female fertility until cessation of treatment. Women may experience a delay in return to ovulation and fertility (conception) following discontinuation of depo-subQ provera 104 [see Warnings and Precautions (5.9)].

8.4 Pediatric Use

Depo-subQ provera 104 is indicated for the prevention of pregnancy and management of endometriosis-associated pain in females of reproductive age. Efficacy is expected to be the same for post-menarchal females under the age of 17 as for users 17 years and older.

Use of depo-subQ provera 104 is associated with significant loss of bone mineral density (BMD). This loss of BMD is of particular concern during adolescence, a critical period of bone accretion. It is unknown if use of depo-subQ provera 104 by female adolescents will reduce peak bone mass and increase the risk for osteoporotic fractures in later life. In a study of adolescent females (12–18 years of age) receiving DMPA-IM for contraception, mean BMD 2 years after starting DMPA-IM decreased 1.9% (spine), 4.3% (total hip), and 4.2% (femoral neck). In those adolescents who used DMPA-IM for more than 2 years, mean BMD at total hip and femoral neck did not return to baseline within 5 years.

Depo-subQ provera 104 is not indicated before menarche.

8.5 Geriatric Use

Depo-subQ provera 104 is not indicated in post-menopausal women.

11 DESCRIPTION

Depo-subQ provera 104 contains medroxyprogesterone acetate (MPA), a derivative of progesterone, as its active ingredient. MPA is a white to off-white, odorless crystalline powder that is stable in air and that melts between 205°C and 209°C. It is freely soluble in chloroform, soluble in acetone and dioxane, sparingly soluble in alcohol and methanol, slightly soluble in ether, and insoluble in water.

The chemical name for MPA is 17-hydroxy-6α-methylpregn-4-ene-3,20-dione 17-acetate. The structural formula is as follows:

Depo-subQ provera 104 for subcutaneous use is available in pre-filled syringes, each containing 0.65 mL (104 mg) of sterile medroxyprogesterone acetate injectable suspension.

Each 0.65 mL contains the following inactive ingredients:

Methylparaben | 1.040 mg
Propylparaben | 0.098 mg
Sodium Chloride | 5.200 mg
Polyethylene Glycol | 18.688 mg
Polysorbate 80 | 1.950 mg
Monobasic Sodium Phosphate H2O | 0.451 mg
Dibasic Sodium Phosphate 12H2O | 0.382 mg
Methionine | 0.975 mg
Povidone | 3.250 mg
Water for Injection | qs

When necessary, the pH is adjusted with sodium hydroxide or hydrochloric acid, or both.

12 CLINICAL PHARMACOLOGY

12.1 Mechanism of Action

Depo-subQ provera 104 inhibits the secretion of gonadotropins, which primarily prevents follicular maturation and ovulation and causes thickening of cervical mucus. These actions contribute to its contraceptive effect.

Suppression of serum estradiol concentrations is likely to be responsible for the therapeutic effect on endometriosis-associated pain.

12.2 Pharmacodynamics

The following laboratory tests are expected to be affected by progestins including depo-subQ provera 104:

- Plasma and urinary steroid levels are decreased (e.g., progesterone, estradiol, pregnanediol, testosterone, cortisol).
- Gonadotropin levels are decreased.
- Sex-hormone-binding-globulin concentrations are decreased.
- Histology specimens may demonstrate changes consistent with progestin effects.

The following laboratory tests may be affected by depo-subQ provera 104, however the clinical significance is unknown:

- Protein-bound iodine and butanol extractable protein-bound iodine may increase.
- T3-uptake values may decrease.
- Coagulation test values for prothrombin (Factor II), and Factors VII, VIII, IX, and X may increase.
- Sulfobromophthalein and other liver function test values may be increased.
- The effects of medroxyprogesterone acetate on lipid metabolism are inconsistent. Both increases and decreases in total cholesterol, triglycerides, low-density lipoprotein (LDL) cholesterol, and high-density lipoprotein (HDL) cholesterol have been observed in studies.

12.3 Pharmacokinetics

The pharmacokinetic parameters of MPA following a single subcutaneous injection of depo-subQ provera 104 in healthy women (n=42) are shown in Table 2 and Figure P.

Table 2. Pharmacokinetic Parameters of MPA after a Single Subcutaneous Injection of depo-subQ provera 104 in Healthy Women
 | Cmax (ng/mL) | Tmax (day) | C91 (ng/mL) | AUC0–91 (ng∙day/mL) | AUC0–∞ (ng∙day/mL) | t½ (day)
Mean | 1.56 | 8.8 | 0.402 | 66.98 | 92.84 | 43
Min | 0.53 | 2.0 | 0.133 | 20.63 | 31.36 | 16
Max | 3.08 | 80.0 | 0.733 | 139.79 | 162.29 | 114
Abbreviations: Cmax=peak serum concentration; Tmax=time when Cmax is observed; C91=serum concentration at 91 days; AUC0–91 and AUC0–∞=area under the concentration-time curve over 91 days or infinity, respectively; t½=terminal half-life.

Following subcutaneous administration of single depo-subQ provera 104 doses ranging from 50 to 150 mg (0.48 and 1.4 times the recommended dose, respectively), the AUC and Cmin (Day 91) increased with higher doses, but there was considerable overlap across dose levels. Serum MPA concentrations at Day 91 increased in a dose proportional manner but Cmax did not appear to increase proportionally with increasing dose. The AUC data were suggestive of dose linearity.

Absorption

Following a single subcutaneous injection of depo-subQ provera 104 in healthy women, serum MPA concentrations reached ≥0.2 ng/mL within 24 hours. The mean Tmax was attained approximately 1 week after injection.

Figure P. Serum Concentration-Time Profile of MPA Mean (SD) after a Single Injection of depo-subQ provera 104 to Healthy Women

In a study to assess accumulation and the achievement of steady state following multiple subcutaneous administrations, trough concentrations of MPA were determined after 6, 12, and 24 months, and in a subset of 8 subjects, bi-weekly concentrations were determined within one dosing interval in the second year of administration. The mean (SD) MPA trough concentrations were 0.67 (0.36) ng/mL (n=157), 0.79 (0.36) ng/mL (n=144), and 0.87 (0.33) ng/mL (n=106) at 6, 12, and 24 months, respectively.

Depo-subQ provera 104 was administered subcutaneously into the anterior thigh or the abdomen to evaluate effects of injection site location on the MPA concentration-time profile. MPA trough concentrations (Cmin; Day 91) were similar for the two injection site locations.

Distribution

Plasma protein binding of MPA averages 86%. MPA binding occurs primarily to serum albumin. No binding of MPA occurs with sex-hormone-binding globulin (SHBG).

Elimination

Metabolism

MPA is extensively metabolized in the liver by P450 enzymes. Its metabolism primarily involves ring A and/or side-chain reduction, loss of the acetyl group, hydroxylation in the 2-, 6-, and 21-positions or a combination of these positions, resulting in more than 10 metabolites.

Excretion

Residual MPA concentrations at the end of the first dosing interval (12 to 14 weeks) of depo-subQ provera 104 were generally below 0.5 ng/mL, consistent with its apparent terminal half-life of ~40 days after subcutaneous administration. Most MPA metabolites were excreted in the urine as glucuronide conjugates with only small amounts excreted as sulfates.

Specific Populations

Racial Groups

There were no significant differences in the pharmacokinetics and/or pharmacodynamics of MPA after subcutaneous administration of depo-subQ provera 104 in African-American, Caucasian, and Asian women.

Effect of Body Weight

Although total MPA exposure was lower in obese women, no dosage adjustment of depo-subQ provera 104 is necessary based on body weight. The effect of body weight on the pharmacokinetics of MPA following a single dose was assessed in a subset of women [n=42, body mass index (BMI) ranged from 18.2 to 46.7 kg/m^2]. The AUC0–91 values for MPA were 71.6, 67.9, and 46.3 ng∙day/mL in women with BMI categories of ≤28 kg/m^2, >28–38 kg/m^2, and >38 kg/m^2, respectively. The mean MPA Cmax was 1.74 ng/mL in women with BMI ≤28 kg/m^2, 1.53 ng/mL in women with BMI >28–38 kg/m^2, and 1.02 ng/mL in women with BMI >38 kg/m^2, respectively. The MPA trough (Cmin) concentrations had a tendency to be lower in women with BMI >38 kg/m^2.

13 NONCLINICAL TOXICOLOGY

13.1 Carcinogenesis, Mutagenesis, Impairment of Fertility

[See Warnings and Precautions (5.3, 5.9)]

14 CLINICAL STUDIES

14.1 Contraception Studies

In three open label clinical studies, depo-SubQ provera 104 (104 mg given every three months subcutaneously), was administered to healthy, sexually-active, nonpregnant women 18 to 49 years of age who desired long-term contraception. In these three studies, no pregnancies were detected among 2042 women treated with depo-subQ provera 104 for up to 1 year. In women less than 36 years of age (at baseline), the Pearl Index pregnancy rate in cycles in which no other contraceptive methods were used, was 0 pregnancies per 100 women-years of use (upper 95% CI = 0.25).

14.2 Endometriosis Studies

The efficacy of depo-subQ provera 104 in the reduction of endometriosis-associated pain in women with the signs and symptoms of endometriosis was demonstrated in two active comparator-controlled studies in pre-menopausal women 18 to 49 years of age with laparoscopically diagnosed endometriosis and persistent endometriosis pain symptoms (i.e., Studies 268 and 270). Each study assessed endometriosis-associated pain over 6 months of treatment and recurrence of symptoms for 12-months post treatment.

Subjects were treated for six months with depo-subQ provera 104 [104 mg given subcutaneously every 3 months (2 injections)] or leuprolide [11.25 mg given subcutaneously every 3 months (2 injections) or 3.75 mg given subcutaneously every month (6 injections)]. Study 268 was conducted in the U.S. and Canada and enrolled 274 subjects (136 subjects received depo-subQ provera 104 and 138 subjects received leuprolide). Study 270 was conducted in South America, Europe, and Asia, and enrolled 299 subjects (153 subjects received depo-subQ provera 104 and 146 subjects received leuprolide).

Reduction in endometriosis pain was evaluated using a modified Biberoglu and Behrman scale that consisted of three patient-reported symptoms (i.e., dysmenorrhea, dyspareunia, and pelvic pain not related to menses) and two signs assessed during pelvic examination (i.e., pelvic tenderness and induration). For each category, a favorable response was defined as improvement of at least 1 unit (severity was assessed on a scale of 0 to 3) relative to baseline score (Figure Q).

Figure Q. Responders at End of Treatment (Month 6 or Last Assessment if Earlier) in Patients with Endometriosis in Studies 268 and 270

Favorable Response = reduction in severity of symptom or sign of ≥1 point on a scale of 0 to 3, as compared to baseline.

Additionally, scores from each of the five categories were combined into a composite score that was considered a global measurement of overall disease improvement. For subjects with baseline scores for each of the 5 categories, a mean decrease of 4 points relative to baseline was considered a clinically meaningful improvement. Across both studies, the mean changes in the composite score met the protocol-defined criterion for improvement for the depo-subQ provera 104 and leuprolide treatment groups.

In the clinical trials, treatment with depo-subQ provera 104 was limited to six months. Data on the persistence of benefit with longer treatment are not available.

14.3 Bone Mineral Density in Women Treated with Depo-medroxyprogesterone acetate for Contraception

In a study that compared changes in bone mineral density (BMD) in adult women using depo-subQ provera 104 or DMPA-IM for contraception, both treatments showed BMD reductions in the lumbar spine, total hip, and femoral neck. Mean percent changes in BMD in depo-subQ provera 104-treated women are shown in Table 3.

Table 3. BMD Mean Percent Change from Baseline in Women Using depo-subQ provera 104 for Contraception
Time on Treatment | Lumbar Spine | Total Hip | Femoral Neck
Time on Treatment | Mean % Change (95% CI) | Mean % Change (95% CI) | Mean % Change (95% CI)
1 year (n=166) | -2.7 (-3.1 to -2.3) | -1.7 (-2.1 to -1.3) | -1.9 (-2.5 to -1.4)
2 years (n=106) | - 4.1 (-4.6 to -3.5) | -3.5 (-4.2 to -2.7) | -3.5 (-4.3 to -2.6)

BMD Recovery Post-Treatment in Women

Given the similar effects on BMD from depo-subQ provera 104 and DMPA-IM described above, BMD recovery post-treatment is also expected to be similar. In a controlled clinical study that compared changes in BMD in adult women using DMPA-IM for contraception or no hormonal contraception, the 2-year post-treatment follow-up demonstrated incomplete recovery of BMD following the last injection of DMPA-IM. Table 4 shows the change in BMD in women after 5 years of treatment with DMPA-IM and in the control group, as well as the extent of BMD recovery in the subset of women for whom 2-year post-treatment data were available.

Table 4. BMD Mean Percent Change from Baseline in Women by Skeletal Site and Cohort (5 Years of Treatment and 2 Years of Follow-Up)
Time in Study | Spine |  | Total Hip |  | Femoral Neck
Time in Study | DMPA-IM [Women who received DMPA-IM for 5 years and were then followed for 2 years post-treatment (total time in study of 7 years).] | Control [Women who did not use hormonal contraception and were followed for 7 years.] | DMPA-IM | Control | DMPA-IM | Control
5 years | -5.38% n=33 | 0.43% n=105 | -5.16% n=21 | 0.19% n=65 | -6.12% n=34 | -0.27% n=106
7 years | -3.13% n=12 | 0.53% n=60 | -1.34% n=7 | 0.94% n=39 | -5.38% n=13 | -0.11% n=63

14.4 Bone Mineral Density Changes in Adolescent Females (12 to 18 years of age) Treated with DMPA-IM

The effect of DMPA-IM on BMD in adolescents is described below, and the effect of depo-subQ provera 104 on BMD in adolescents is expected to be similar. The impact of DMPA-IM use for up to 240 weeks (4.6 years) was evaluated in an open-label non-randomized clinical study in 389 adolescent females (12 to 18 years of age). Use of DMPA-IM was associated with a significant decline from baseline in BMD.

Partway through the trial, DMPA-IM administration was stopped (at 120 weeks). The mean number of injections per DMPA-IM user was 9.3. Table 5 summarizes the study findings. The decline in BMD at total hip and femoral neck was greater with longer duration of use. The mean decrease in BMD at 240 weeks was more pronounced at total hip (-6.4%) and femoral neck (-5.4%) compared to lumbar spine (-2.1%).

Adolescents in the untreated cohort had an increase in BMD during the period of growth following menarche. However, the two cohorts were not matched at baseline for age, gynecologic age, race, BMD, and other factors that influence the rate of acquisition of BMD.

Table 5. BMD Mean Percent Change from Baseline in Adolescents Receiving ≥4 Injections per 60-week Period, by Skeletal Site and Cohort
Duration of Treatment | DMPA-IM (150 mg) |  | Unmatched, Untreated Cohort
Duration of Treatment | N | Mean % Change | N | Mean % Change
Total Hip BMD
Week 60 (1.2 years) | 113 | -2.75 | 166 | 1.22
Week 120 (2.3 years) | 73 | -5.40 | 109 | 2.19
Week 240 (4.6 years) | 28 | -6.40 | 84 | 1.71
Femoral Neck BMD
Week 60 | 113 | -2.96 | 166 | 1.75
Week 120 | 73 | -5.30 | 108 | 2.83
Week 240 | 28 | -5.40 | 84 | 1.94
Lumbar Spine BMD
Week 60 | 114 | -2.47 | 167 | 3.39
Week 120 | 73 | -2.74 | 109 | 5.28
Week 240 | 27 | -2.11 | 84 | 6.40

BMD Recovery Post-Treatment in Adolescents

Longer duration of treatment and smoking were associated with less recovery of BMD following the last injection of DMPA-IM. Table 6 shows the extent of recovery of BMD up to 60 months post-treatment for adolescents who received DMPA-IM for two years or less compared to more than two years. Post-treatment follow-up showed that, in adolescents treated for more than two years, only lumbar spine BMD recovered to baseline levels after treatment was discontinued. Adolescents treated with DMPA-IM for more than two years did not recover to their baseline BMD level at the femoral neck and total hip even up to 60 months post-treatment. Adolescents in the untreated cohort gained BMD throughout the trial period [see Warnings and Precautions (5.1)].

Table 6. BMD Recovery (Months Post-Treatment) in Adolescents by Years of DMPA-IM Use (2 Years or Less vs. More than 2 Years)
Duration of Treatment (Months) | 2 Years or Less |  | More than 2 Years
Duration of Treatment (Months) | N | Mean % Change from baseline | N | Mean % Change from baseline
Total Hip BMD
End of Treatment | 49 | -1.5% | 49 | -6.2%
12 M post-treatment | 33 | -1.4% | 24 | -4.6%
24 M post-treatment | 18 | 0.3% | 17 | -3.6%
36 M post-treatment | 12 | 2.1% | 11 | -4.6%
48 M post-treatment | 10 | 1.3% | 9 | -2.5%
60 M post-treatment | 3 | 0.2% | 2 | -1.0%
Femoral Neck BMD
End of Treatment | 49 | -1.6% | 49 | -5.8%
12 M post-treatment | 33 | -1.4% | 24 | -4.3%
24 M post-treatment | 18 | 0.5% | 17 | -3.8%
36 M post-treatment | 12 | 1.2% | 11 | -3.8%
48 M post-treatment | 10 | 2.0% | 9 | -1.7%
60 M post-treatment | 3 | 1.0% | 2 | -1.9%
Lumbar Spine BMD
End of Treatment | 49 | -0.9% | 49 | -3.5%
12 M post-treatment | 33 | 0.4% | 23 | -1.1%
24 M post-treatment | 18 | 2.6% | 17 | 1.9%
36 M post-treatment | 12 | 2.4% | 11 | 0.6%
48 M post-treatment | 10 | 6.5% | 9 | 3.5%
60 M post-treatment | 3 | 6.2% | 2 | 5.7%

14.5 Bone Fracture Incidence in Women Treated with Depo-medroxyprogesterone acetate for Contraception

A retrospective cohort study to assess the association between DMPA-IM injection and the incidence of bone fractures was conducted in 312,395 female contraceptive users in the UK. The incidence rates of fracture were compared between DMPA-IM users and contraceptive users who had no recorded use of DMPA-IM. The Incident Rate Ratio (IRR) for any fracture during the follow-up period (mean=5.5 years) was 1.41 (95% CI 1.35, 1.47). It is not known if this is due to DMPA-IM use or to other related lifestyle factors that have a bearing on fracture rate.

In the study, when cumulative exposure to DMPA-IM was calculated, the fracture rate in users who received fewer than 8 injections was higher than that in women who received 8 or more injections. However, it is not clear that cumulative exposure, which may include periods of intermittent use separated by periods of non-use, is a useful measure of risk, as compared to exposure measures based on continuous use.

There were very few osteoporotic fractures (fracture sites known to be related to low BMD) in the study overall, and the incidence of osteoporotic fractures was not found to be higher in DMPA-IM users compared to non-users.

Importantly, this study could not determine whether use of DMPA-IM has an effect on fracture rate later in life. Given the similar effects on BMD from depo-subQ provera 104 and DMPA-IM described above, bone fracture incidence may also be expected to be similar.

14.6 Bone Mineral Density in Women Treated with depo-SubQ provera 104 for Endometriosis

In two clinical studies of 573 adult women with endometriosis, the BMD effects of 6 months of depo-subQ provera 104 treatment (104 mg subcutaneously every 3 months) were compared to 6 months of leuprolide treatment (either 11.25 mg given subcutaneously every 3 months or 3.75 mg given subcutaneously every month). Subjects were then observed after treatment completion, for an additional 12 months. See Table 7 for the results.

Table 7. BMD Mean Percent Change from Baseline after Therapy for Endometriosis with depo-subQ provera 104 or Leuprolide for 6 Months, and 6- and 12-Months Post-Therapy (Studies 268 and 270 Combined)
Time of BMD Measurement | Lumbar Spine |  |  |  | Total Hip
Time of BMD Measurement | depo-subQ provera 104 |  | Leuprolide |  | depo-subQ provera 104 |  | Leuprolide
Time of BMD Measurement | N | Mean % Change | N | Mean % Change | N | Mean % Change | N | Mean % Change
Month 6 of treatment (End of Treatment) | 208 | -1.20 | 229 | -4.10 | 207 | -0.03 | 227 | -1.83
6 months post-treatment | 168 | -1.06 | 180 | -2.75 | 169 | -0.05 | 181 | -1.59
12 months post-treatment | 124 | -0.54 | 133 | -1.48 | 125 | 0.39 | 134 | -1.15

15 REFERENCES

1. Li CI, Beaber EF, Tang MCT et al. Effect of Depo-Medroxyprogesterone Acetate on Breast Cancer Risk among Women 20 to 44 years of Age. Cancer Research 2012; 72:2028-2035.
2. Paul C, Skegg DCG, Spears GFS. Depot medroxyprogesterone (Depo-Provera) and risk of breast cancer. Br Med J 1989; 299:759-62.

16 HOW SUPPLIED/STORAGE AND HANDLING

16.1 How Supplied

Depo-subQ provera 104 medroxyprogesterone acetate injectable suspension (104 mg/0.65 mL) is available in a single dose, disposable pre-filled syringe and is packaged with a 26-gauge × 3/8-inch Terumo SurGuard® needle.

NDC 0009-4709-13

16.2 Storage

Store at controlled room temperature 20° C to 25° C (68° F to 77°F) [see USP]. Do not refrigerate.

17 PATIENT COUNSELING INFORMATION

Advise the patient to read the FDA-approved patient labeling (Patient Information).

Loss of Bone Mineral Density

Advise the patient that the use of depo-subQ provera 104 decreases BMD [see Warnings and Precautions (5.1)].

Arterial and Venous Thromboembolic Disorders

Advise the patient that serious arterial and venous thrombotic events have been seen in women treated with depot medroxyprogesterone acetate (DMPA) [see Warnings and Precautions (5.2)].

Anaphylaxis

Counsel patients on the importance of seeking urgent medical attention if they experience symptoms of anaphylaxis [see Warnings and Precautions (5.6)].

Ectopic Pregnancy

Advise patients to tell their healthcare professional right away if they become pregnant or experience severe abdominal pain to exclude a diagnosis of ectopic pregnancy [see Warnings and Precautions (5.5)].

Bleeding Irregularities

Advise patients at the beginning of treatment that their menstrual cycle may be disrupted, resulting in irregular and unpredictable bleeding or spotting. Explain that bleeding and spotting irregularities usually decrease to the point of amenorrhea as treatment with depo-subQ provera 104 continues and does not require other therapy [see Warnings and Precautions (5.12)].

Delayed Return of Ovulation and Fertility

Advise patients that return to ovulation and fertility is likely to be delayed after stopping depo-subQ provera 104 [see Warnings and Precautions (5.9)].

Risks of Breast Cancer

Counsel patients about the possible increased risk of breast cancer in women who use depo-subQ provera 104 [see Warnings and Precautions (5.3)].

Meningioma

Counsel patients with a history of meningioma about the possible risk of worsening meningioma [see Warnings and Precautions (5.4)].

Depression

Counsel patients about the possible risk of depression and mood disorders. Advise patients with a history of depression or who are receiving treatment for depression to be alert to any mood changes or worsening of their depression. Counsel patients to follow up with their healthcare professional accordingly [see Warnings and Precautions (5.10)].

Risk of Hyperglycemia in Patients with Diabetes

Advise diabetic patients that some patients receiving progestins may exhibit a decrease in glucose tolerance and hyperglycemia [see Warnings and Precautions (5.13)].

Liver Dysfunction

Advise patients to seek medical advice if they experience symptoms of liver problems such as jaundice [see Warnings and Precautions (5.14)].

Fluid Retention

Counsel patients with conditions that may be influenced by fluid retention to inform their healthcare professional if they experience symptoms of fluid retention [see Warnings and Precautions (5.7)].

Injection Site Reactions

Counsel patients that injection site reactions including site dimpling, scarring or discoloration may occur [see Warnings and Precautions (5.11)].

Sexually Transmitted Infections

Counsel patients that depo-subQ provera 104 does not protect against HIV infection (AIDS) and other sexually transmitted infections [see Warnings and Precautions (5.15)].

Drug Interactions

Counsel patients to contact their healthcare professional if they start a medication that is a CYP3A enzyme inducer [see Drug Interactions (7)]. Advise patients that taking a medication that is a CYP3A enzyme inducer may require using a back-up or alternate contraceptive method.

This product's labeling may have been updated. For the most recent prescribing information, please visit www.pfizer.com.

LAB-0295-19.0

PATIENT INFORMATION
DEPO-SUBQ PROVERA 104®
(deh-poh' sub-cue' pro-ver-ah' one-oh-four)
(medroxyprogesterone acetate injectable suspension)
for subcutaneous use

WHAT IS THE MOST IMPORTANT INFORMATION I SHOULD KNOW ABOUT depo-subQ provera 104?

Use of depo-subQ provera 104 may cause you to lose calcium stored in your bones. The longer you use depo-subQ provera 104 the more calcium you are likely to lose. The calcium may not return completely once you stop using depo-subQ provera 104.

Loss of calcium may cause weak, porous bones (osteoporosis) that could increase the risk that your bones might break, especially after menopause. It is not known whether your risk of developing osteoporosis may be greater if you are a teenager when you start to use depo-subQ provera 104.

You should use depo-subQ provera 104 long-term (for example, more than 2 years) only if other methods of birth control or other treatments for endometriosis pain are not right for you.

Depo-subQ provera 104 does not protect you from HIV (AIDS) and other sexually transmitted infections (STIs).

WHAT IS depo-subQ provera 104?

Depo-subQ provera 104 is a drug for birth control. It also helps relieve pain related to endometriosis (en-do-ME-tree-OH-sis). Symptoms of endometriosis arise when cells normally inside your uterus grow outside the uterus. The cells respond to menstrual cycle hormones, and may cause painful periods, pelvic pain, and painful sex.

Depo-subQ provera 104 contains a hormone called medroxyprogesterone acetate (MPA). It is given as a shot (injection) every 3 months. Three months is the same as 12 to 14 weeks.

HOW WELL DOES depo-subQ provera 104 WORK FOR PREVENTING PREGNANCY?

When you use depo-subQ provera 104 correctly, the chance of getting pregnant is very low. In studies, no women became pregnant during the year they used depo-subQ provera 104 injection.

The list below estimates the chances of getting pregnant using different types of birth control. The numbers are based on typical use. Typical use includes people who use the method correctly and people who use the method incorrectly. The list shows the number of women out of 100 women who will likely get pregnant if they use the method for 1 year.

Method | Typical Chance of Getting Pregnant in 1 year (Number of pregnancies in 100 women)
Shot Implant Female sterilization Male sterilization IUD (copper IUD and levonorgestrel IUD) | Less than 1
Pill | 5
Condom alone (male) | 14
Withdrawal | 19
Diaphragm with spermicides | 20
Condom alone (female) | 21
Periodic abstinence | 25
Spermicides alone | 26
Vaginal sponge or Cervical cap with spermicide | 20 to 40

HOW WILL I GET depo-subQ provera 104?

Depo-subQ provera 104 is given as a shot just under the skin on your thigh or belly. You get it once every 3 months.

For Birth Control

First shot:

Your healthcare professional will want to be sure that you are not pregnant before you get your first shot. Normally, you get the shot by the 5th day from the START of your menstrual period. You get it whether or not you are still bleeding.

If you are breast-feeding, you may have your first shot as early as 6 weeks after you deliver your baby.

After the first shot:

It is very important to keep getting depo-subQ provera 104 every 3 months. If you wait more than 14 weeks between shots, you could become pregnant. Your healthcare professional must make sure you are not pregnant before you get your next shot.

When you get your shot, make an appointment for your next shot. Mark it on your calendar.

If you need a birth control method for more than two years, your healthcare professional may ask you to have a test of your bones or ask you to switch to another birth control method before continuing depo-subQ provera 104, especially if you have other risks for weak bones.

For Endometriosis

If you have regular periods, you will get depo-subQ provera 104 the same way as described above for birth control. If your periods have stopped or are not regular, your healthcare professional must test to make sure you are not pregnant before you get your first shot.

It is not recommended that you receive depo-subQ provera 104 for treatment of endometriosis for longer than 2 years. If your painful symptoms return after stopping treatment, your healthcare professional should ask you to have a test of your bones before restarting treatment.

WHAT IF I MISS A SHOT?

If you miss a shot, or wait longer than 14 weeks between shots, you could get pregnant. The longer you wait, the greater the risk of getting pregnant.
Talk with your healthcare professional to find out when to restart depo-subQ provera 104. You should be tested to be sure you are not pregnant.
Use another kind of non-hormonal birth control, such as condoms, until you start depo-subQ provera 104 again.

DO NOT TAKE depo-subQ provera 104 IF YOU…

- Have any unexplained vaginal bleeding
- Have or have ever had breast cancer or think you have breast cancer
- Ever had serious blood clots, such as blood clots in your legs (deep venous thrombophlebitis), lungs (pulmonary embolism), heart (heart attack), or head (stroke)
- Have liver disease
- Are allergic to anything in depo-subQ provera 104. There is a list of what is in depo-subQ provera 104 at the end of this leaflet.

BEFORE TAKING depo-subQ provera 104

Your healthcare professional may do a physical examination and check your blood and urine.

Tell your healthcare professional about all your medical conditions.

Most importantly, tell your healthcare professional if you:

- Are pregnant or might be pregnant. You should not get depo-subQ provera 104 if you are pregnant.
- Plan to become pregnant in the next year. After you stop getting depo-subQ provera 104, it takes time for your body to be able to get pregnant. It can be as early as 1 week after the last shot wears off. Most likely it will take up to 1 year or longer for you to get pregnant.
- Have or have ever had breast cancer, or think you have breast cancer
- Have breast cancer in your family
- Have an abnormal mammogram (breast X-ray), lumps in your breast, or bleeding from your nipples
- Have or have ever had a type of usually benign brain tumor called a meningioma
- Have irregular, light, or heavy menstrual periods
- Have or had any of the following medical problems:
  - Kidney problems
  - High blood pressure
  - Migraine headaches
  - Asthma
  - Seizures
  - Diabetes, or if it runs in your family
  - Depression
  - Heart attack, stroke, or blood clots
  - Bone disease
  - Anorexia nervosa (an eating disorder)
  - A strong family history of osteoporosis
  - Use of a drug that can lower the amount of calcium in bones (drugs for epilepsy or steroids)
  - Drinking a lot of alcohol or smoking a lot

It is important to see your healthcare professional regularly if you have any of these conditions.

Some medicines may make depo-subQ provera 104 less effective at preventing pregnancy, including those listed below:

- Bosentan (used to treat pulmonary arterial hypertension)
- Efavirenz, etravirine (HIV medicines)
- Modafinil (used to improve wakefulness)
- Mitotane (used to treat adrenal cortical carcinoma)
- Phenytoin, carbamazepine, phenobarbital (used to treat seizures)
- Rifampin (an antibiotic)
- St. John's Wort (herbal medicinal product)

Tell your healthcare professional about all the medicines you take. This includes prescription and over-the-counter medicines, vitamins, and herbal products.

WHAT ELSE SHOULD I KNOW ABOUT TAKING depo-subQ provera 104?

Other Birth Control. If you can't take birth control pills or can't use a birth control patch or ring, you may be able to use depo-subQ provera 104. Ask your healthcare professional.

Pregnancy. When you take depo-subQ provera 104 every 3 months, your chance of getting pregnant is very low. You could miss a period or have a light period and not be pregnant. If you miss 1 or 2 periods and think you might be pregnant, see your healthcare professional as soon as possible.

You should not use depo-subQ provera 104 if you are pregnant. However, depo-subQ provera 104 taken by accident during pregnancy does not seem to cause birth defects.

Pregnancy in your fallopian tubes (Ectopic Pregnancy). If you have severe pain low in your belly, tell your healthcare professional right away. Infrequently, a baby may start to grow outside the uterus, most often in the tubes.

Nursing a baby. Wait at least 6 weeks after your baby is born to start depo-subQ provera 104. You can use depo-subQ provera 104 if you are nursing.

It does not lower the amount of milk you can make.
It can pass through breast milk into your baby, but it is not harmful.

Blood or urine tests. Depo-subQ provera 104 may affect blood or urine test results. Tell your healthcare professional you are taking depo-subQ provera 104 if you are going to have blood or urine tests.

Liver problems. Your healthcare professional may stop depo-subQ provera 104 if you have liver problems. Some signs of liver problems are yellow skin or eyes, feeling like you have the flu, feeling more tired than usual, and itching. Tell your healthcare professional if you have these symptoms.

WHAT ARE THE MOST SERIOUS RISKS OF depo-subQ provera 104?

Losing calcium from your bones. Depo-subQ provera 104 use may decrease the amount of calcium in your bones. The longer you use depo-subQ provera 104, the more calcium you are likely to lose. This increases the risk of your bones weakening if you use depo-subQ provera 104 continuously for a long time (for example, if you use depo-subQ provera 104 for more than 2 years). The loss of calcium may increase your risk of osteoporosis and broken bones, particularly after your menopause.

Calcium is generally added to the bones during teenage years. The decrease of calcium in your bones is of most concern if you are a teenager or have the following risk factors:

- Bone disease
- Anorexia nervosa (an eating disorder)
- A strong family history of osteoporosis
- Using a drug that can lower the amount of calcium in bones (drugs for epilepsy or steroids), or
- Drinking a lot of alcohol or smoking a lot

If you need a birth control method for more than 2 years, your healthcare professional may ask you to have a test of your bones or ask you to switch to another birth control method before continuing depo-subQ provera 104, especially if you have other risks for weak bones. When depo-subQ provera 104 is stopped, the calcium in your bones begins to come back. The lost calcium may not return completely once you stop using depo-subQ provera 104.

Abnormal or very heavy bleeding. If you start having very heavy or very long periods, tell your healthcare professional.

Allergic reaction. Allergic reactions to depo-subQ provera 104 have been reported. If you have hives, problems breathing, swelling of the face, mouth, tongue, or neck, or just do not feel right after your shot, call your healthcare professional or go to the Emergency Room right away.

Serious blood clots. Call your healthcare professional immediately if you:

- Have sharp chest pain, cough blood, or suddenly have trouble breathing
- Have a sudden severe headache with vomiting, blindness or trouble talking, weakness, or numbness in an arm or leg, or get dizzy or faint
- Have swelling or severe pain in your leg

Depression. If you suffer from depression or have a history of depression, inform your healthcare professional if you notice any worsening of your depression while taking depo-subQ provera 104.

Meningioma (a type of usually benign brain tumor). Possible increased risk for growth of a meningioma, primarily when the product is used for a long time.

WHAT ARE COMMON SIDE EFFECTS OF depo-subQ provera 104?

The most common side effects are:

- Changes in your monthly periods. You may not know when you will bleed, your periods may not be regular, you may have heavy bleeding, or you may have spotting. You may have more days of bleeding during the first 2 or 3 months after you start depo-subQ provera 104. Over time, you may have less and less bleeding. Many women stop having periods by the end of 1 year. Your periods will come back eventually after you stop using depo-subQ provera 104.
- Headache.
- Weight gain. In studies, women gained an average of 3 to 4 pounds during the first year they used depo-subQ provera 104. After 2 years of using depo-subQ provera 104, women gained an average of 7 to 8 pounds. Some women gained more, some gained less, some lost, and some stayed the same. Weight changes beyond 2 years of use with depo-subQ provera 104 have not been studied. Women who used a similar birth control product for 5 years gained on average 5 pounds more than women who did not use a hormone contraceptive product.
- Skin reaction where you got the shot. Lumps, skin dimpling, or pain may occur. Scarring and discoloration are uncommon, but may happen. If there is swelling or your skin gets hot, has pus or looks bruised 1 or more days after your shot, call your healthcare professional.

Women using depo-subQ provera 104 for birth control or endometriosis had these less common side effects: Vaginal inflammation, vaginal thrush, abdominal pain, urinary tract infections, acne, depression, less sex drive, nausea, back pain, breast pain/tenderness, fatigue, anxiety, being irritable, dizziness, hot flushes and fluid retention.

If you feel you are having other side effects, talk with your healthcare professional.

DOES depo-subQ provera 104 CAUSE CANCER?

There have been several studies of women who use birth control like depo-subQ provera 104.

- Women who use depo-subQ provera 104 may have a slightly increased risk of breast cancer compared to non-users.
- The risk of cancer of the ovary, liver, or cervix did not change.

WHAT IF I WANT TO BECOME PREGNANT?

Plan ahead. The effect of depo-subQ provera 104 can last for a long time after you stop getting shots. Although you may be able to get pregnant quickly, it is more likely to take a year or longer after your last shot before you get pregnant.

It's best to see your healthcare professional for a pre-pregnancy check-up. Your healthcare professional may also tell you to take a vitamin called folic acid every day if you are planning to become pregnant.

GENERAL ADVICE ABOUT depo-subQ provera 104

For more information about depo-subQ provera 104, ask your healthcare professional or pharmacist.

WHAT IS IN depo-subQ provera 104?

Active ingredient: medroxyprogesterone acetate.
Inactive ingredients: methylparaben, propylparaben, sodium chloride, polyethylene glycol, polysorbate 80, monobasic sodium phosphate∙H2O, dibasic sodium phosphate∙12H2O, methionine, povidone, water for shot. When necessary, the pH is adjusted with sodium hydroxide or hydrochloric acid, or both.

This product's labeling may have been updated. For the most recent prescribing information, please visit www.pfizer.com.

LAB-0298-12.0
Revised December 2025

PRINCIPAL DISPLAY PANEL - 0.65 mL Syringe Label

PAA229214

depo-subQ
provera 104®
(medroxyprogesterone acetate) injectable
suspension (104 mg/0.65 mL for subcutaneous use)

104 mg/0.65 mL

0.65 mL Single Dose Syringe
Store at 20°C to 25°C (68°F to 77°F).
Do not refrigerate.
Shake vigorously before use.

Pharmacia & Upjohn Company LLC

LOT/EXP:

PRINCIPAL DISPLAY PANEL - 0.65 mL Syringe Carton

NDC 0009-4709-13

Single Dose 0.65 mL Prefilled Syringe

depo-subQ provera 104®
(medroxyprogesterone acetate) injectable suspension
(104 mg/0.65 mL for subcutaneous use)

104 mg/0.65 mL

Pfizer

Distributed by
Pharmacia & Upjohn Company LLC
A Subsidiary of Pfizer Inc.
New York, NY 10011

Rx only